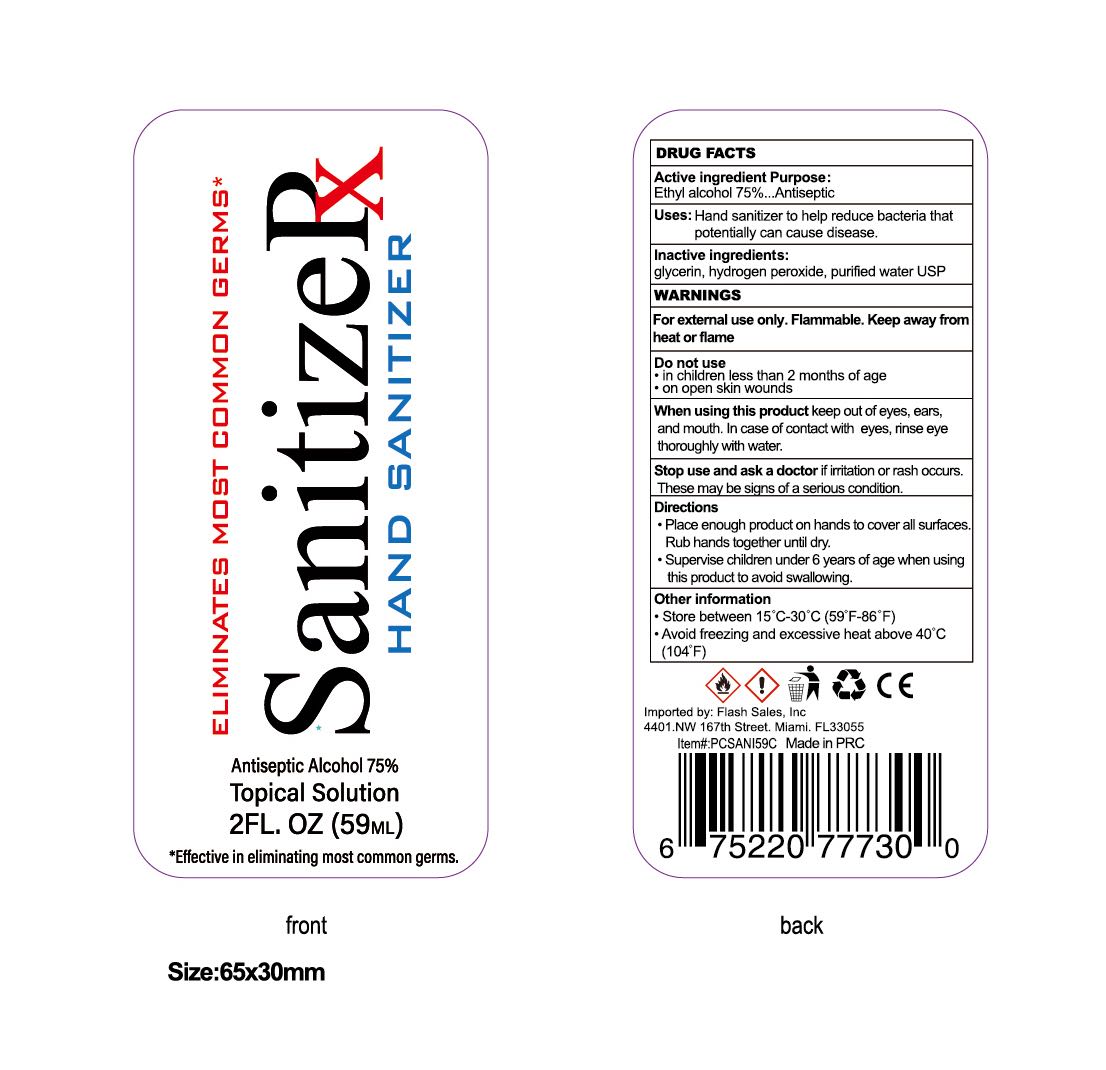 DRUG LABEL: SanitizeRx
NDC: 78414-004 | Form: GEL
Manufacturer: Guangzhou caolvxiang Biotechnology Co.,Ltd
Category: otc | Type: HUMAN OTC DRUG LABEL
Date: 20200901

ACTIVE INGREDIENTS: ALCOHOL 75 mL/100 mL
INACTIVE INGREDIENTS: 1,1-BIS(TERT-BUTYLPEROXY)CYCLOHEXANE; WATER; GLYCERIN

78414-004
HAND SANITIZER GEL

Active Ingredient(s)

Ethyl Alcohol75%

Purpose

Antiseptic

Use

Hand sanitizer to help reduce bacteria that potentially can cause disease

Warnings

For external use only. Flammable. Keep away from heat or flame

Keep out of reach of children If swallowed get medical help or contact a Poison Control Center right away

When using this product keep out of eyes, ears, and mouth. In case of contact with eyesrinse eye thoroughly with water.

Stop use and ask a doctor if irritation or rash occurs. These may be signs of a serious condition

Do not use

/

WHEN USING SECTION

Keep out of reach of children If swallowed get medical help or contact a Poison Control Center right away

When using this product keep out of eyes, ears, and mouth. In case of contact with eyesrinse eye thoroughly with water.

Stop use and ask a doctor if irritation or rash occurs. These may be signs of a serious condition

STOP USE

Stop use and ask a doctor if irritation or rash occurs. These may be signs of a serious condition

Keep out of reach of children If swallowed get medical help or contact a Poison Control Center right away

Directions

Place enough product on hands to cover all surfaces. Rub hands together until dry
Supervise children under 6 years of age when using this product to avoid swallowing

Other information

Store between 15C-30C(59F-86F)
Avoid freezing and excessive heat above 40C(104F)

Inactive ingredients

purified water
glycerin
Hydrogen peroxide